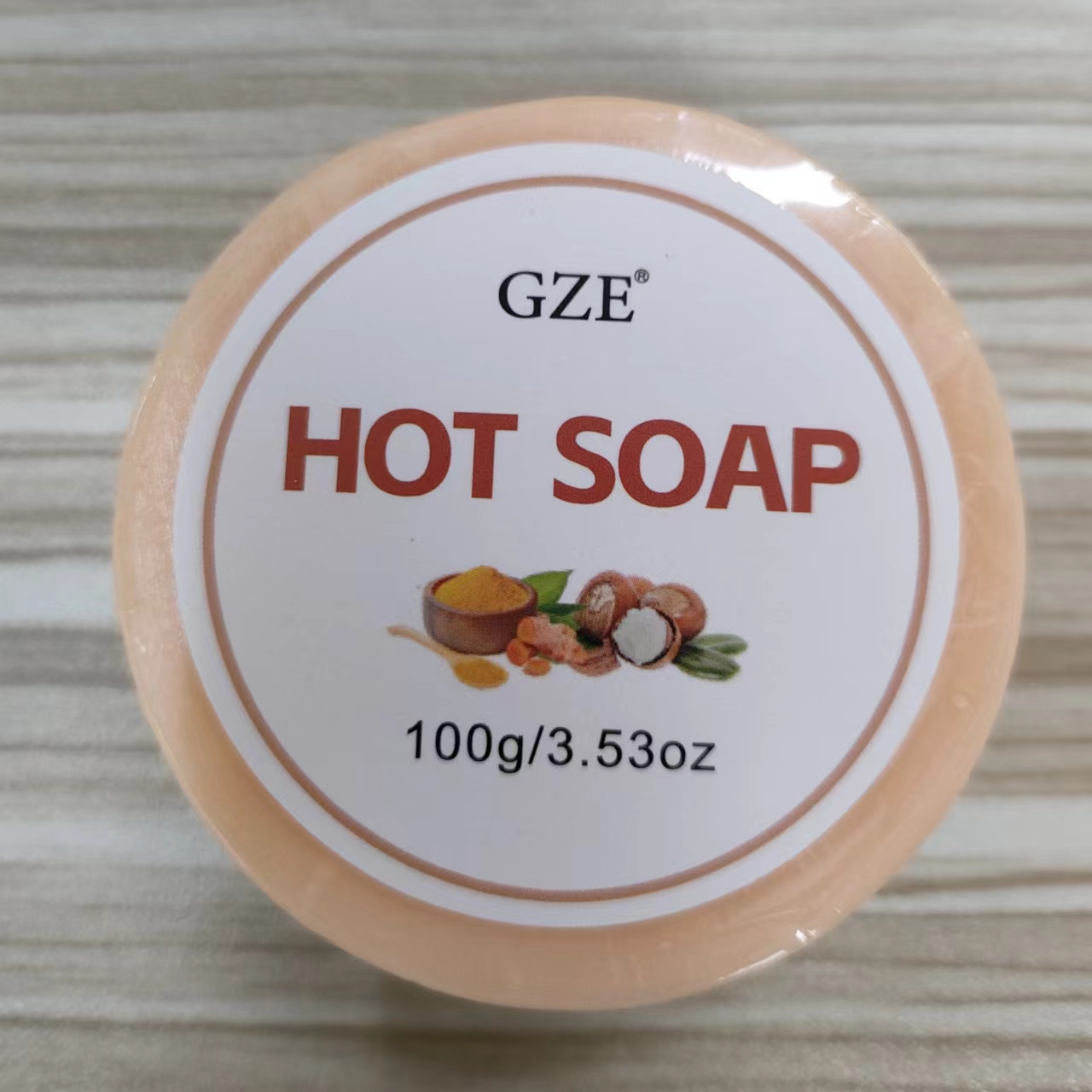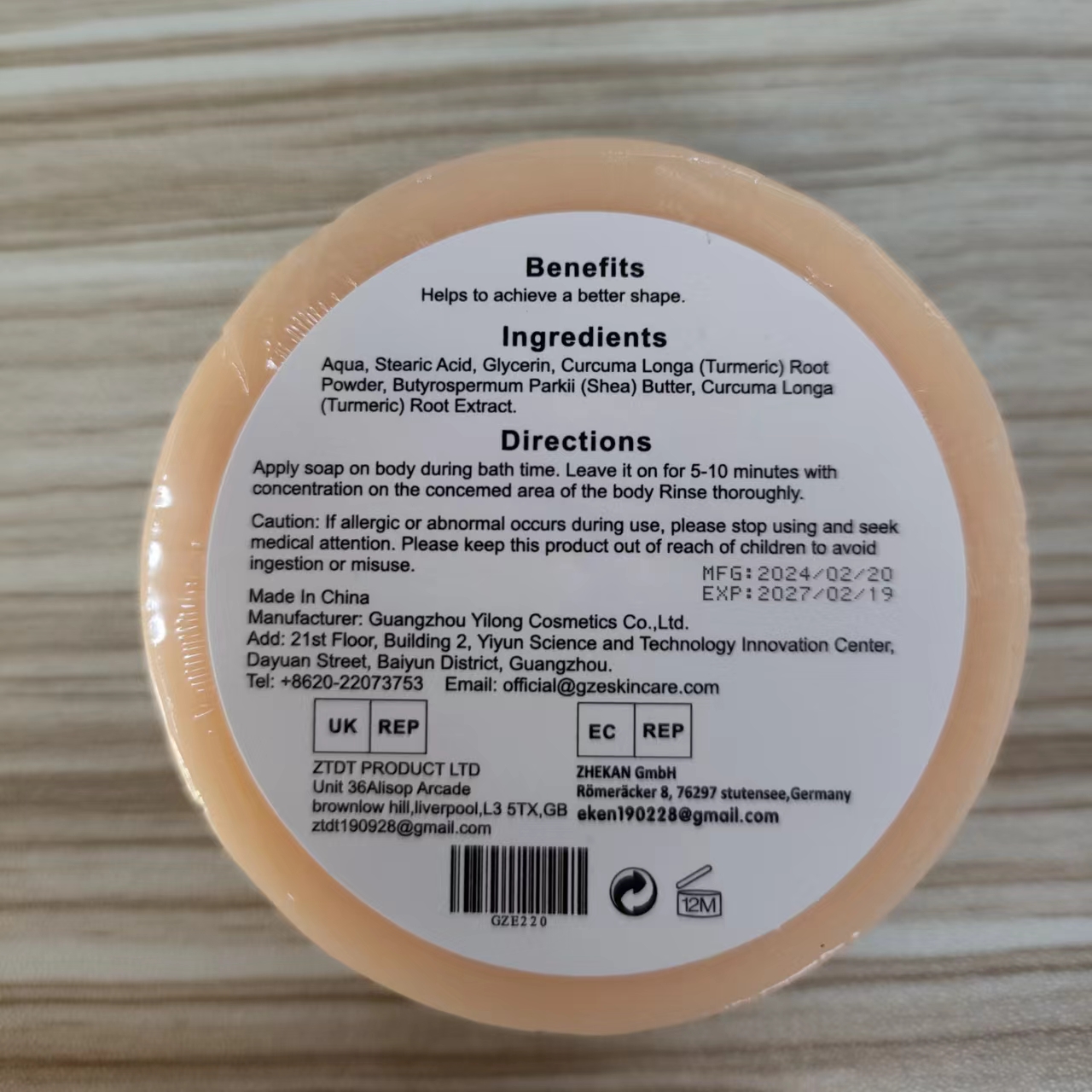 DRUG LABEL: Gze HotSoap
NDC: 83566-220 | Form: SOAP
Manufacturer: Guangzhou Yilong Cosmetics Co., Ltd
Category: otc | Type: HUMAN OTC DRUG LABEL
Date: 20240719

ACTIVE INGREDIENTS: TURMERIC OIL 10 g/100 g; TURMERIC 15 g/100 g
INACTIVE INGREDIENTS: WATER; GLYCERIN; BUTYROSPERMUM PARKII (SHEA) BUTTER UNSAPONIFIABLES; STEARIC ACID

Gze hot soap

ACTIVE INGREDIENT

Turmeric

Turmeric oil

INACTIVE INGREDIENT

Aqua

Stearic Acid

Glycerin

Butyrospermum Parkii (Shea) Butter

PURPOSE

Helps to achieve a better shape.

INDICATIONS AND USAGE

Apply soap on body during bath time. Leave it on for 5-10 minutes with concentration on the concemed area of the body Rinse thoroughly.

WARNINGS

For external use only.

Stop use and ask a doctor if rash occurs.

Do not use on damaged or broken skin.

When using this product keep out of eyes. Rinse with water to remove.

Keep out of reach of children. If swallowed, get medical help or contact a Poison Control Center right away.

DOSAGE AND ADMINISTRATION

Apply soap on body during bath time. Leave it on for 5-10 minutes with concentration on the concemed area of the body Rinse thoroughly.